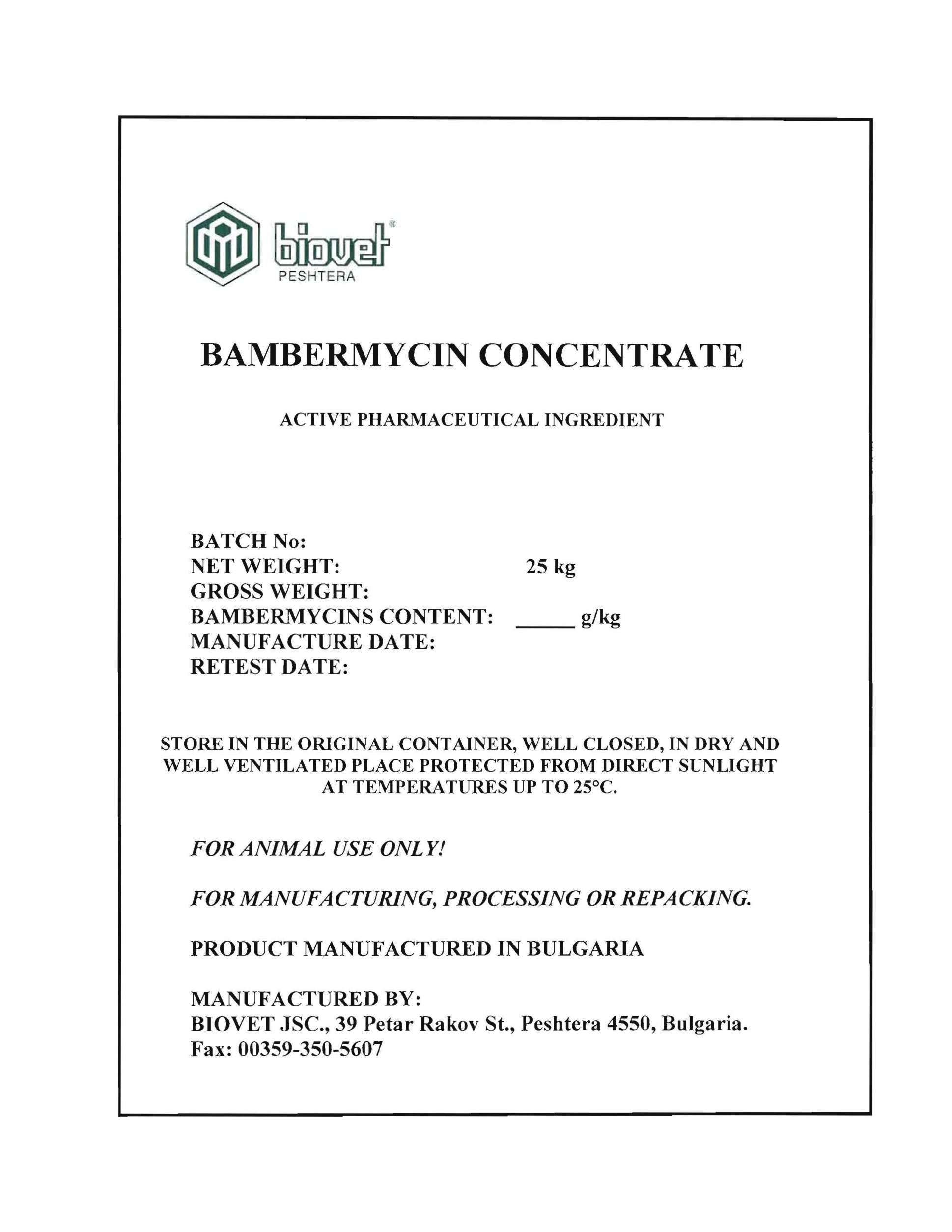 DRUG LABEL: Bambermycin Concentrate
NDC: 11311-886 | Form: POWDER
Manufacturer: Biovet Joint Stock Company
Category: other | Type: BULK INGREDIENT - ANIMAL DRUG
Date: 20200130

ACTIVE INGREDIENTS: BAMBERMYCINS .080 kg/.080 kg

BAMBERMYCINS CONCENTRATE